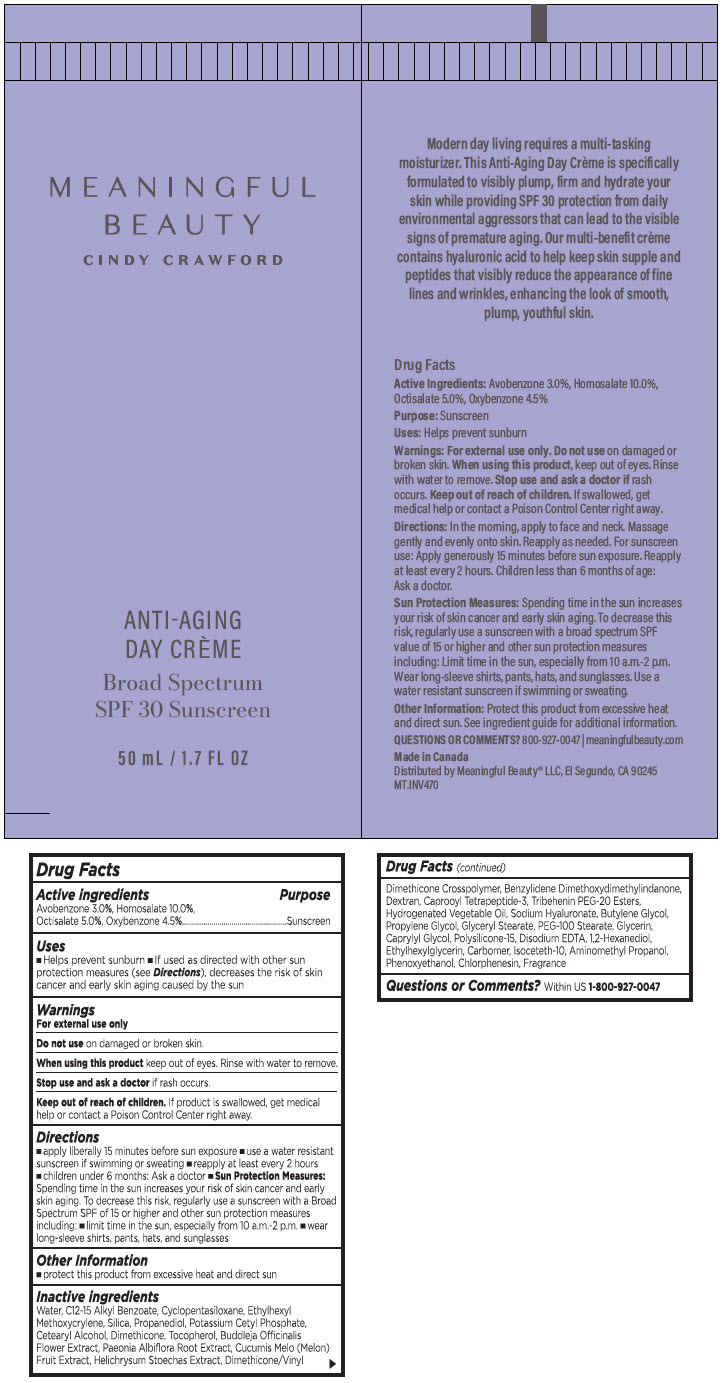 DRUG LABEL: Meaningful Beauty Cindy Crawford Anti-Aging Day Creme with Environmental Protection Broad Spectrum SPF 30
NDC: 84068-001 | Form: CREAM
Manufacturer: Meaningful Beauty, LLC
Category: otc | Type: HUMAN OTC DRUG LABEL
Date: 20250115

ACTIVE INGREDIENTS: Avobenzone 3 mg/100 mL; Homosalate 10 mg/100 mL; Octisalate 5 mg/100 mL; Oxybenzone 4.5 mg/100 mL
INACTIVE INGREDIENTS: water; ALKYL (C12-15) BENZOATE; CYCLOMETHICONE 7; Ethylhexyl Methoxycrylene; SILICON DIOXIDE; Propanediol; Potassium Cetyl Phosphate; CETOSTEARYL ALCOHOL; Dimethicone; Tocopherol; BUDDLEJA OFFICINALIS FLOWER; PAEONIA LACTIFLORA ROOT; MUSKMELON; HELICHRYSUM STOECHAS FLOWER; DIMETHICONE/VINYL DIMETHICONE CROSSPOLYMER (SOFT PARTICLE); Benzylidene Dimethoxydimethylindanone; DEXTRAN 1; Caprooyl Tetrapeptide-3; Tribehenin PEG-20 Esters; HYDROGENATED PALM OIL; HYALURONATE SODIUM; Butylene Glycol; Propylene Glycol; GLYCERYL MONOSTEARATE; PEG-100 Stearate; Glycerin; Caprylyl Glycol; Polysilicone-15; EDETATE DISODIUM; 1,2-Hexanediol; Ethylhexylglycerin; CARBOMER HOMOPOLYMER, UNSPECIFIED TYPE; Isoceteth-10; AMINOMETHYLPROPANOL; Phenoxyethanol; Chlorphenesin

Meaningful Beauty Cindy Crawford Anti-Aging Day Creme with Environmental Protection Broad Spectrum SPF 30

Drug Facts

Active ingredients

Avobenzone 3.0%, Homosalate 10.0%, Octisalate 5.0%, Oxybenzone 4.5%

Purpose

Sunscreen

Uses

- Helps prevent sunburn
- If used as directed with other sun protection measures (see Directions), decreases the risk of skin cancer and early skin aging caused by the sun

Warnings

For external use only

Do not use on damaged or broken skin.

When using this product keep out of eyes. Rinse with water to remove.

Stop use and ask a doctor if rash occurs.

Keep out of reach of children. If product is swallowed, get medical help or contact a Poison Control Center right away.

Directions

- apply liberally 15 minutes before sun exposure
- use a water resistant sunscreen if swimming or sweating
- reapply at least every 2 hours
- children under 6 months: Ask a doctor
- Sun Protection Measures: Spending time in the sun increases your risk of skin cancer and early skin aging. To decrease this risk, regularly use a suncreen with a Broad Spectrum SPF of 15 or higher and other sun protection measures including:
  - limit time in the sun, especially from 10 a.m.-2 p.m.
  - wear long-sleeve shirts, pants, hats, and sunglasses

Other Information

- protect this product from excessive heat and direct sun

Inactive ingredients

Water, C12-15 Alkyl Benzoate, Cyclopentasiloxane, Ethylhexyl Methoxycrylene, Silica, Propanediol, Potassium Cetyl Phosphate, Cetearyl Alcohol, Dimethicone, Tocopherol, Buddleja Officinalis Flower Extract, Paeonia Albiflora Root Extract, Cucumis Melo (Melon) Fruit Extract, Helichrysum Stoechas Extract, Dimethicone/Vinyl Dimethicone Crosspolymer, Benzylidene Dimethoxydimethylindanone, Dextran, Caprooyl Tetrapeptide-3, Tribehenin PEG-20 Esters, Hydrogenated Vegetable Oil, Sodium Hyaluronate, Butylene Glycol, Propylene Glycol, Glyceryl Stearate, PEG-100 Stearate, Glycerin, Caprylyl Glycol, Polysilicone-15, Disodium EDTA, 1,2-Hexanediol, Ethylhexylglycerin, Carbomer, Isoceteth-10, Aminomethyl Propanol, Phenoxyethanol, Chlorphenesin, Fragrance

Questions or Comments?

Within US 1-800-927-0047

Distributed by Meaningful Beauty® LLC, El Segundo, CA 90245

PRINCIPAL DISPLAY PANEL - 50 mL Tube Label

MEANINGFUL
BEAUTY
CINDY CRAWFORD

ANTI-AGING
DAY CRÈME

Broad Spectrum
SPF 30 Sunscreen

50 mL / 1.7 FL OZ